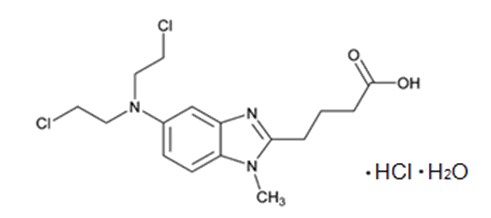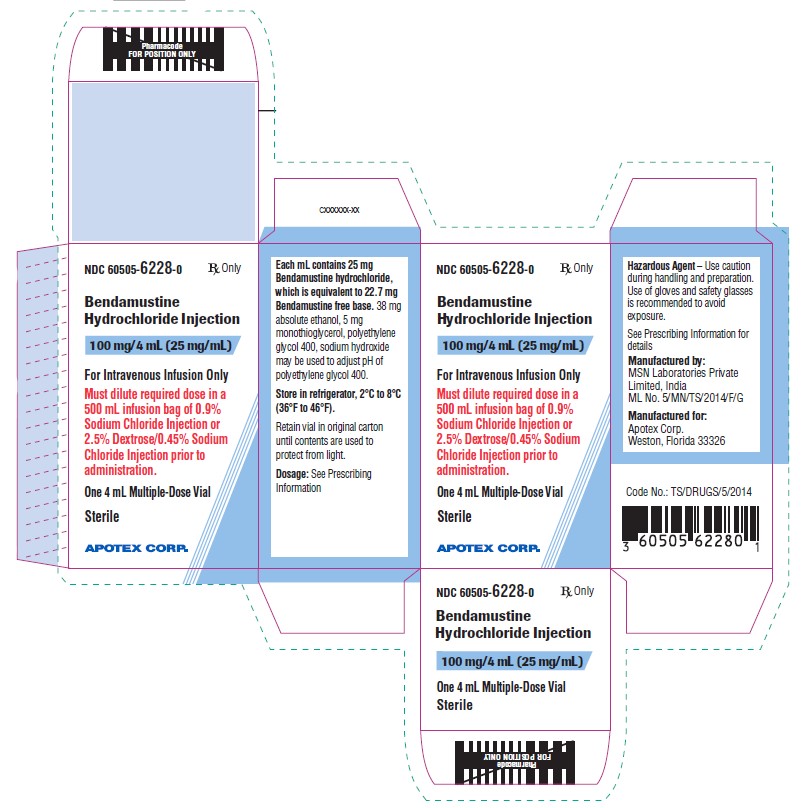 DRUG LABEL: Bendamustine Hydrochloride
NDC: 60505-6228 | Form: INJECTION, SOLUTION
Manufacturer: Apotex Corp
Category: prescription | Type: HUMAN PRESCRIPTION DRUG LABEL
Date: 20250916

ACTIVE INGREDIENTS: BENDAMUSTINE HYDROCHLORIDE 25 mg/1 mL
INACTIVE INGREDIENTS: MONOTHIOGLYCEROL 5 mg/1 mL; POLYETHYLENE GLYCOL, UNSPECIFIED; SODIUM HYDROXIDE  0.08 mg/1 mL; ALCOHOL 38 mg/1 mL

HIGHLIGHTS OF PRESCRIBING INFORMATION

These highlights do not include all the information needed to use BENDAMUSTINE HYDROCHLORIDE INJECTION safely and effectively. See full prescribing information for BENDAMUSTINE HYDROCHLORIDE INJECTION.
BENDAMUSTINE HYDROCHLORIDE injection, for intravenous use
Initial U.S. Approval: 2008

RECENT MAJOR CHANGES SECTION

Indications and Usage, Chronic Lymphocytic Leukemia (CLL) indication removed (1.1) 04/2024

Dosage and Administration, Dosing Instructions for CLL removed (2.1) 04/2024

1 INDICATIONS AND USAGE

Bendamustine hydrochloride injection is an alkylating drug indicated for treatment of adult patients with:

- Indolent B-cell non-Hodgkin lymphoma (NHL) that has progressed during or within six months of treatment with rituximab or a rituximab-containing regimen. (1)

2 DOSAGE AND ADMINISTRATION

For NHL:

• 120 mg/m^2 infused intravenously over 60 minutes on Days 1 and 2 of a 21-day cycle, up to 8 cycles (2.1)

3 DOSAGE FORMS AND STRENGTHS

Injection: 100 mg/4mL (25 mg/mL) in a multiple-dose vial. (3)

4 CONTRAINDICATIONS

Bendamustine hydrochloride injection is contraindicated in patients with a history of a hypersensitivity reaction to bendamustine, polyethylene glycol 400, absolute ethanol, sodium hydroxide and monothioglycerol. Reactions to bendamustine hydrochloride have included anaphylaxis and anaphylactoid reactions. (4, 5.4)

5 WARNINGS AND PRECAUTIONS

- Myelosuppression: Delay or reduce dose and restart treatment based on ANC and platelet count recovery. (5.1)
- Infections: Monitor for fever and other signs of infection or reactivation of infections and treat promptly. (5.2)
- Progressive multifocal leukoencephalopathy (PML): Monitor for new or worsening neurological, cognitive or behavioral signs or symptoms suggestive of PML. (5.3)
- Anaphylaxis and Infusion Reactions: Severe anaphylactic reactions have occurred. Monitor clinically and discontinue drug for severe reactions. Pre-medicate in subsequent cycles for milder reactions. (5.4)
- Tumor Lysis Syndrome: May lead to acute renal failure and death; anticipate and use supportive measures in patients at high risk. (5.5)
- Skin Reactions: Discontinue for severe skin reactions. Cases of SJS, DRESS and TEN, some fatal, have been reported. (5.6)
- Hepatotoxicity: Monitor liver chemistry tests prior to and during treatment. (5.7)
- Other Malignancies: Pre-malignant and malignant diseases have been reported. (5.8)
- Extravasation Injury: Take precautions to avoid extravasation, including monitoring intravenous infusion site during and after administration. (5.9)
- Embryo-Fetal Toxicity: Can cause fetal harm. Advise females of reproductive potential and males with female partners of reproductive potential of the potential risk to a fetus and to use an effective method of contraception. (5.10, 8.1, 8.3)

6 ADVERSE REACTIONS

- Adverse reactions (frequency >5%) during infusion and within 24 hours post-infusion are nausea and fatigue. (6.1)
- Most common adverse reactions (≥15%) for NHL are lymphopenia, leukopenia, anemia, neutropenia, thrombocytopenia, nausea, fatigue, vomiting, diarrhea, pyrexia, constipation, anorexia, cough, headache, weight decreased, dyspnea, rash, and stomatitis.(6.1).

To report SUSPECTED ADVERSE REACTIONS, contact Apotex Corp. at 1-800-706-5575 or FDA at 1-800-FDA-1088 or www.fda.gov/medwatch.

7 DRUG INTERACTIONS

Consider alternative therapies that are not CYP1A2 inducers or inhibitors during treatment with bendamustine hydrochloride injection. (7.1)

8 USE IN SPECIFIC POPULATIONS

- Lactation: Advise not to breastfeed. (8.2)
- Infertility: May impair fertility. (8.3)
- Renal Impairment: Do not use in patients with creatinine clearance <30 mL/min. (8.6)
- Hepatic Impairment: Do not use in patients with total bilirubin 1.5-3 x ULN and AST or ALT 2.5-10 x ULN, or total bilirubin >3 x ULN. (8.7)

FULL PRESCRIBING INFORMATION

1 INDICATIONS AND USAGE

Non-Hodgkin Lymphoma (NHL)

Bendamustine hydrochloride injection is indicated for the treatment of adult patients with indolent B-cell non-Hodgkin lymphoma that has progressed during or within six months of treatment with rituximab or a rituximab-containing regimen.

2 DOSAGE AND ADMINISTRATION

2.1 Dosing Instructions for NHL

Recommended Dosage:

The recommended dosage is 120 mg/m^2 administered intravenously over 60 minutes on Days 1 and 2 of a 21-day cycle, up to 8 cycles.

Dose Delays, Dosage Modifications and Reinitiation of Therapy for NHL:

Delay bendamustine hydrochloride injection administration in the event of a Grade 4 hematologic toxicity or clinically significant greater or equal to Grade 2 non-hematologic toxicity. Once non-hematologic toxicity has recovered to ≤ Grade 1 and/or the blood counts have improved [Absolute Neutrophil Count (ANC) ≥ 1 x 10^9/L, platelets ≥ 75 x 10^9/L], reinitiate bendamustine hydrochloride injection at the discretion of the treating physician. In addition, consider dose reduction. [see Warnings and Precautions (5.1)]

Dosage modifications for hematologic toxicity: for Grade 4 toxicity, reduce the dose to 90 mg/m^2 on Days 1 and 2 of each cycle; if Grade 4 toxicity recurs, reduce the dose to 60 mg/m^2 on Days 1 and 2 of each cycle.

Dosage modifications for non-hematologic toxicity: for Grade 3 or greater toxicity, reduce the dose to 90 mg/m^2 on Days 1 and 2 of each cycle; if Grade 3 or greater toxicity recurs, reduce the dose to 60 mg/m^2 on Days 1 and 2 of each cycle.

2.2 Preparation for Intravenous Administration

Bendamustine hydrochloride injection is a hazardous drug. Follow applicable special handling and disposal procedures.^1

Bendamustine hydrochloride injection is in a multiple-dose vial. Bendamustine hydrochloride injection is a clear and colorless to yellow solution. Store bendamustine hydrochloride injection at recommended refrigerated storage conditions (2°C to 8°C or 36°F to 46°F). When refrigerated the contents may freeze. Allow the vial to reach room temperature (15°C to 30°C or 59°F to 86°F) prior to use. Observe the contents of the vial for any visible solid or particulate matter and discoloration. Do not use the product if solid or particulate matter is observed after reaching room temperature.

Intravenous Infusion

Aseptically withdraw the volume needed for the required dose from the 25 mg/mL solution as per Table A below and immediately transfer to a 500 mL infusion bag of one of the following diluents:

- 0.9% Sodium Chloride Injection, USP; or

- 2.5% Dextrose/0.45% Sodium Chloride Injection, USP.

The resulting final concentration of bendamustine hydrochloride injection in the infusion bag should be within 0.05 mg/mL to 0.7 mg/mL. After transferring, thoroughly mix the contents of the infusion bag. The admixture should be a clear and colorless to slightly yellow solution. Use either 0.9% Sodium Chloride Injection, USP, or 2.5% Dextrose/0.45% Sodium Chloride Injection, USP, for dilution, as outlined above. No other diluents have been shown to be compatible.

Table A: Volume (mL) of Bendamustine Hydrochloride Injection required for dilution into 500 mL of 0.9% Sodium Chloride Injection, USP, or 0.45% Sodium Chloride/2.5% Dextrose Injection, USP for a given dose (mg/m^2) and Body Surface Area (m^2)

Body Surface Area (m^2) | Volume of Bendamustine Hydrochloride Injection to withdraw (mL)
 | 120 mg/m^2 | 90 mg/m^2 | 60 mg/m^2
1 | 4.8 | 3.6 | 2.4
1.1 | 5.3 | 4 | 2.6
1.2 | 5.8 | 4.3 | 2.9
1.3 | 6.2 | 4.7 | 3.1
1.4 | 6.7 | 5 | 3.4
1.5 | 7.2 | 5.4 | 3.6
1.6 | 7.7 | 5.8 | 3.8
1.7 | 8.2 | 6.1 | 4.1
1.8 | 8.6 | 6.5 | 4.3
1.9 | 9.1 | 6.8 | 4.6
2 | 9.6 | 7.2 | 4.8
2.1 | 10.1 | 7.6 | 5
2.2 | 10.6 | 7.9 | 5.3
2.3 | 11 | 8.3 | 5.5
2.4 | 11.5 | 8.6 | 5.8
2.5 | 12 | 9 | 6
2.6 | 12.5 | 9.4 | 6.2
2.7 | 13 | 9.7 | 6.5
2.8 | 13.4 | 10.1 | 6.7
2.9 | 13.9 | 10.4 | 7
3 | 14.4 | 10.8 | 7.2

Parenteral drug products should be inspected visually for particulate matter and discoloration prior to administration whenever solution and container permit. Any unused solution should be discarded according to institutional procedures for antineoplastics.

2.3 Admixture Stability

Bendamustine hydrochloride injection contains no antimicrobial preservative. The admixture should be prepared as close as possible to the time of patient administration.

If diluted with 0.9% Sodium Chloride Injection, USP, or 2.5% Dextrose/0.45% Sodium Chloride Injection, USP, the final admixture is stable for 24 hours when stored refrigerated (2°C to 8°C or 36°F to 46°F) or for 3 hours when stored at room temperature (15°C to 30°C or 59°F to 86°F) and room light. Administration of diluted bendamustine hydrochloride injection must be completed within this period of time.

Bendamustine hydrochloride injection is supplied in a multiple-dose vial. Retain the partially used vial in original package to protect from light and store refrigerated (2°C to 8°C or 36°F to 46°F) if additional dose withdrawal from the same vial is intended.

2.4 Stability of Partially Used Vials (Needle Punched Vials)

Bendamustine hydrochloride injection is supplied as a multiple-dose vial. Although it does not contain any antimicrobial preservative, bendamustine hydrochloride injection is bacteriostatic. The partially used vials are stable for up to 28 days when stored in its original carton under refrigeration (2°C to 8°C or 36°F to 46°F). Each vial is not recommended for more than a total of six (6) dose withdrawals.

After first use, store the partially used vial in original carton at 2°C to 8°C (36°F to 46°F), and then discard after 28 days.

3 DOSAGE FORMS AND STRENGTHS

Injection: 100 mg/4 mL (25 mg/mL) as a clear and colorless to yellow solution in a multiple-dose vial.

4 CONTRAINDICATIONS

Bendamustine hydrochloride injection is contraindicated in patients with a known hypersensitivity (e.g., anaphylactic and anaphylactoid reactions) to bendamustine, polyethylene glycol 400, absolute ethanol, sodium hydroxide and monothioglycerol. [see Warnings and Precautions (5.4)]

5 WARNINGS AND PRECAUTIONS

5.1 Myelosuppression

Bendamustine hydrochloride caused severe myelosuppression (Grade 3 to 4) in 98% of patients in the two NHL studies [see Adverse Reactions (6.1)]. Three patients (2%) died from myelosuppression-related adverse reactions; one each from neutropenic sepsis, diffuse alveolar hemorrhage with Grade 3 thrombocytopenia, and pneumonia from an opportunistic infection (CMV).

Bendamustine hydrochloride injection causes myelosuppression. Monitor complete blood counts, including leukocytes, platelets, hemoglobin (Hgb), and neutrophils frequently. In the clinical trials, blood counts were monitored every week initially. Hematologic nadirs were observed predominantly in the third week of therapy. Myelosuppression may require dose delays and/or subsequent dose reductions if recovery to the recommended values has not occurred by the first day of the next scheduled cycle. Prior to the initiation of the next cycle of therapy, the ANC should be ≥ 1 x 10^9/L and the platelet count should be ≥ 75 x 10^9/L. [see Dosage and Administration (2.2)].

5.2 Infections

Infection, including pneumonia, sepsis, septic shock, hepatitis and death has occurred in adult and pediatric patients in clinical trials and in postmarketing reports for bendamustine hydrochloride [see Adverse Reactions (6.1, 6.2)]. Patients with myelosuppression following treatment with bendamustine hydrochloride are more susceptible to infections. Advise patients with myelosuppression following bendamustine hydrochloride injection treatment to contact a physician immediately if they have symptoms or signs of infection.

Patients treated with bendamustine hydrochloride injection are at risk for reactivation of infections including (but not limited to) hepatitis B, cytomegalovirus, Mycobacterium tuberculosis, and herpes zoster. Patients should undergo appropriate measures (including clinical and laboratory monitoring, prophylaxis, and treatment) for infection and infection reactivation prior to administration.

5.3 Progressive Multifocal Leukoencephalopathy (PML)

Progressive multifocal leukoencephalopathy (PML), including fatal cases, have occurred following treatment with bendamustine hydrochloride, primarily in combination with rituximab or obinutuzumab [see Adverse Reactions (6.2)]. Consider PML in the differential diagnosis in patients with new or worsening neurological, cognitive or behavioral signs or symptoms. If PML is suspected, withhold bendamustine hydrochloride injection treatment and perform appropriate diagnostic evaluations. Consider discontinuation or reduction of any concomitant chemotherapy or immunosuppressive therapy in patients who develop PML.

5.4 Anaphylaxis and Infusion Reactions

Infusion reactions to bendamustine hydrochloride have occurred commonly in clinical trials [see Adverse Reactions (6.1)]. Symptoms include fever, chills, pruritus and rash. In rare instances severe anaphylactic and anaphylactoid reactions have occurred, particularly in the second and subsequent cycles of therapy. Monitor clinically and discontinue drug for severe reactions. Ask patients about symptoms suggestive of infusion reactions after their first cycle of therapy. Patients who experience Grade 3 or worse allergic-type reactions should not be rechallenged. Consider measures to prevent severe reactions, including antihistamines, antipyretics and corticosteroids in subsequent cycles in patients who have experienced Grade 1 or 2 infusion reactions. Discontinue bendamustine hydrochloride injection for patients with Grade 4 infusion reactions. Consider discontinuation for Grade 3 infusion reactions as clinically appropriate considering individual benefits, risks, and supportive care.

5.5 Tumor Lysis Syndrome

Tumor lysis syndrome associated with bendamustine hydrochloride has occurred in patients in clinical trials and in post-marketing reports [see Adverse Reactions (6.1)]. The onset tends to be within the first treatment cycle of bendamustine hydrochloride and, without intervention, may lead to acute renal failure and death. Preventive measures include vigorous hydration and close monitoring of blood chemistry, particularly potassium and uric acid levels. Allopurinol has also been used during the beginning of bendamustine hydrochloride therapy. However, there may be an increased risk of severe skin toxicity when bendamustine hydrochloride and allopurinol are administered concomitantly [see Warnings and Precautions (5.6)].

5.6 Skin Reactions

Fatal and serious skin reactions have been reported with bendamustine hydrochloride treatment in clinical trials and postmarketing safety reports, including toxic skin reactions [Stevens-Johnson Syndrome (SJS), toxic epidermal necrolysis (TEN), and drug reaction with eosinophilia and systemic symptoms (DRESS), bullous exanthema, and rash [see Adverse Reactions (6.1 and 6.2)]. Events occurred when bendamustine hydrochloride was given as a single agent and in combination with other anticancer agents or allopurinol.

Where skin reactions occur, they may be progressive and increase in severity with further treatment. Monitor patients with skin reactions closely. If skin reactions are severe or progressive, withhold or discontinue bendamustine hydrochloride injection.

5.7 Hepatotoxicity

Fatal and serious cases of liver injury have been reported with bendamustine hydrochloride injection [see Adverse Reactions (6.1)]. Combination therapy, progressive disease or reactivation of hepatitis B were confounding factors in some patients [see Warnings and Precautions (5.2)]. Most cases were reported within the first three months of starting therapy. Monitor liver chemistry tests prior to and during bendamustine hydrochloride injection therapy.

5.8 Other Malignancies

There are reports of pre-malignant and malignant diseases that have developed in patients who have been treated with bendamustine hydrochloride, including myelodysplastic syndrome, myeloproliferative disorders, acute myeloid leukemia, bronchial carcinoma, and non-melanoma skin cancer, including basal cell carcinoma and squamous cell carcinoma [see Adverse Reactions (6.2)].

Monitor patients for the development of secondary malignancies. Perform dermatologic evaluations during and after treatment with bendamustine hydrochloride injection.

5.9 Extravasation Injury

Bendamustine hydrochloride extravasations have been reported in postmarketing resulting in hospitalizations from erythema, marked swelling, and pain [see Adverse Reactions (6.2)]. Assure good venous access prior to starting bendamustine hydrochloride injection infusion and monitor the intravenous infusion site for redness, swelling, pain, infection, and necrosis during and after administration of bendamustine hydrochloride injection.

5.10 Embryo-Fetal Toxicity

Based on findings from animal reproduction studies and the drug’s mechanism of action, bendamustine hydrochloride injection can cause fetal harm when administered to a pregnant woman. Single intraperitoneal doses of bendamustine (that approximated the maximum recommended human dose based on body surface area) to pregnant mice and rats during organogenesis caused adverse developmental outcomes, including an increase in resorptions, skeletal and visceral malformations, and decreased fetal body weights. Advise pregnant women of the potential risk to a fetus. Advise females of reproductive potential to use an effective method of contraception during treatment with bendamustine hydrochloride injection and for 6 months after the last dose. Advise males with female partners of reproductive potential to use effective contraception during treatment with bendamustine hydrochloride injection and for 3 months after the last dose [see Use in Specific Populations (8.1, 8.3) and Clinical Pharmacology (12.1)] .

6 ADVERSE REACTIONS

The following clinically significant serious adverse reactions are discussed in greater detail in other sections of the prescribing information.

- Myelosuppression [see Warnings and Precautions (5.1)]
- Infections [see Warnings and Precautions (5.2)]
- Progressive Multifocal Leukoencephalopathy [see Warnings and Precautions (5.3)]
- Anaphylaxis and Infusion Reactions [see Warnings and Precautions (5.4)]
- Tumor Lysis Syndrome [see Warnings and Precautions (5.5)]
- Skin Reactions [see Warnings and Precautions (5.6)]
- Hepatotoxicity [see Warnings and Precautions (5.7)]
- Other Malignancies [see Warnings and Precautions (5.8)]
- Extravasation Injury [see Warnings and Precautions (5.9)]

6.1 Clinical Trials Experience

Because clinical trials are conducted under widely varying conditions, adverse reaction rates observed in the clinical trials of a drug cannot be directly compared to rates in the clinical trials of another drug and may not reflect the rates observed in practice.

Clinical Trials Experience in NHL

The data described below reflect exposure to bendamustine hydrochloride in 176 patients with indolent B-cell NHL treated in two single-arm studies. The population was 31 to 84 years of age, 60% male, and 40% female. The race distribution was 89% White, 7% Black, 3% Hispanic, 1% other, and <1% Asian. These patients received bendamustine hydrochloride at a dose of 120 mg/m^2 intravenously on Days 1 and 2 for up to eight 21-day cycles.

The adverse reactions occurring in at least 5% of the NHL patients, regardless of severity, are shown in Table 3. The most common non-hematologic adverse reactions (≥30%) were nausea (75%), fatigue (57%), vomiting (40%), diarrhea (37%) and pyrexia (34%). The most common non-hematologic Grade 3 or 4 adverse reactions (≥5%) were fatigue (11%), febrile neutropenia (6%), and pneumonia, hypokalemia and dehydration, each reported in 5% of patients.

Table 3: Non-Hematologic Adverse Reactions Occurring in at Least 5% of NHL Patients Treated with Bendamustine Hydrochloride by System Organ Class and Preferred Term (N=176)

Body System | Number (%) of patients*
Adverse Reaction | All Grades | Grade 3/4
Total number of patients with at least 1 adverse reaction | 176 (100) | 94 (53)
Cardiac disorders
Tachycardia | 13 (7) | 0
Gastrointestinal disorders
Nausea | 132 (75) | 7 (4)
Vomiting | 71 (40) | 5 (3)
Diarrhea | 65 (37) | 6 (3)
Constipation | 51 (29) | 1 (<1)
Stomatitis | 27 (15) | 1 (<1)
Abdominal pain | 22 (13) | 2 (1)
Dyspepsia | 20 (11) | 0
Gastroesophageal reflux disease | 18 (10) | 0
Dry mouth | 15 (9) | 1 (<1)
Abdominal pain upper | 8 (5) | 0
Abdominal distension | 8 (5) | 0
General disorders and administration site conditions
Fatigue | 101 (57) | 19 (11)
Pyrexia | 59 (34) | 3 (2)
Chills | 24 (14) | 0
Edema peripheral | 23 (13) | 1 (<1)
Asthenia | 19 (11) | 4 (2)
Chest pain | 11 (6) | 1 (<1)
Infusion site pain | 11 (6) | 0
Pain | 10 (6) | 0
Catheter site pain | 8 (5) | 0
Infections and infestations
Herpes zoster | 18 (10) | 5 (3)
Upper respiratory tract infection | 18 (10) | 0
Urinary tract infection | 17 (10) | 4 (2)
Sinusitis | 15 (9) | 0
Pneumonia | 14 (8) | 9 (5)
Febrile neutropenia | 11 (6) | 11 (6)
Oral candidiasis | 11 (6) | 2 (1)
Nasopharyngitis | 11 (6) | 0
Investigations
Weight decreased | 31 (18) | 3 (2)
Metabolism and nutrition disorders
Anorexia | 40 (23) | 3 (2)
Dehydration | 24 (14) | 8 (5)
Decreased appetite | 22 (13) | 1 (<1)
Hypokalemia | 15 (9) | 9 (5)
Musculoskeletal and connective tissue disorders
Back pain | 25 (14) | 5 (3)
Arthralgia | 11 (6) | 0
Pain in extremity | 8 (5) | 2 (1)
Bone pain | 8 (5) | 0
Nervous system disorders
Headache | 36 (21) | 0
Dizziness | 25 (14) | 0
Dysgeusia | 13 (7) | 0
Psychiatric disorders
Insomnia | 23 (13) | 0
Anxiety | 14 (8) | 1 (<1)
Depression | 10 (6) | 0
Respiratory, thoracic and mediastinal disorders
Cough | 38 (22) | 1 (<1)
Dyspnea | 28 (16) | 3 (2)
Pharyngolaryngeal pain | 14 (8) | 1 (<1)
Wheezing | 8 (5) | 0
Nasal congestion | 8 (5) | 0
Skin and subcutaneous tissue disorders
Rash | 28 (16) | 1 (<1)
Pruritus | 11 (6) | 0
Dry skin | 9 (5) | 0
Night sweats | 9 (5) | 0
Hyperhidrosis | 8 (5) | 0
Vascular disorders
Hypotension | 10 (6) | 2 (1)

*Patients may have reported more than 1 adverse reaction.

NOTE: Patients counted only once in each preferred term category and once in each system organ class category.

Hematologic toxicities, based on laboratory values and CTC grade, in NHL patients treated in both single arm studies combined are described in Table 4. Clinically important chemistry laboratory values that were new or worsened from baseline and occurred in >1% of patients at Grade 3 or 4, in NHL patients treated in both single arm studies combined were hyperglycemia (3%), elevated creatinine (2%), hyponatremia (2%), and hypocalcemia (2%).

Table 4: Incidence of Hematology Laboratory Abnormalities in Patients Who Received Bendamustine Hydrochloride in the NHL Studies

Hematology Variable | Percent of Patients
Hematology Variable | All Grades | Grade 3/4
Lymphocytes Decreased | 99 | 94
Leukocytes Decreased | 94 | 56
Hemoglobin Decreased | 88 | 11
Neutrophils Decreased | 86 | 60
Platelets Decreased | 86 | 25

In both studies, serious adverse reactions, regardless of causality, were reported in 37% of patients receiving bendamustine hydrochloride. The most common serious adverse reactions occurring in ≥5% of patients were febrile neutropenia and pneumonia. Other important serious adverse reactions reported in clinical trials and/or post-marketing experience were acute renal failure, cardiac failure, hypersensitivity, skin reactions, pulmonary fibrosis, and myelodysplastic syndrome.

Serious drug-related adverse reactions reported in clinical trials included myelosuppression, infection, pneumonia, tumor lysis syndrome and infusion reactions. Adverse reactions occurring less frequently but possibly related to bendamustine hydrochloride treatment were hemolysis, dysgeusia/taste disorder, atypical pneumonia, sepsis, herpes zoster, erythema, dermatitis, and skin necrosis.

6.2 Postmarketing Experience

The following adverse reactions have been identified during post-approval use of bendamustine hydrochloride. Because these reactions are reported voluntarily from a population of uncertain size, it is not always possible to reliably estimate their frequency or establish a causal relationship to drug exposure.

Blood and lymphatic systems disorders: Pancytopenia

Cardiovascular disorders: Atrial fibrillation, congestive heart failure (some fatal), myocardial infarction (some fatal), palpitation

General disorders and administration site conditions: Injection site reactions (including phlebitis, pruritus, irritation, pain, swelling), infusion site reactions (including phlebitis, pruritus, irritation, pain, swelling)

Immune system disorders: Anaphylaxis

Infections and infestations: Pneumocystis jirovecii pneumonia, progressive multifocal leukoencephalopathy (PML)

Renal and urinary disorders: Nephrogenic diabetes insipidus (NDI)

Respiratory, thoracic and mediastinal disorders: Pneumonitis

Skin and subcutaneous tissue disorders: Drug reaction with eosinophilia and systemic symptoms (DRESS), non-melanoma skin cancer (NMSC), Stevens-Johnson syndrome (SJS), toxic epidermal necrolysis (TEN).

7 DRUG INTERACTIONS

7.1 Effect of Other Drugs on Bendamustine Hydrochloride Injection

CYP1A2 Inhibitors

The coadministration of bendamustine hydrochloride injection with CYP1A2 inhibitors may increase bendamustine plasma concentrations and may result in increased incidence of adverse reactions with bendamustine hydrochloride injection [see Clinical Pharmacology (12.3)]. Consider alternative therapies that are not CYP1A2 inhibitors during treatment with bendamustine hydrochloride injection.

CYP1A2 Inducers

The coadministration of bendamustine hydrochloride injection with CYP1A2 inducers may decrease bendamustine plasma concentrations and may result in decreased efficacy of bendamustine hydrochloride injection [see Clinical Pharmacology (12.3)]. Consider alternative therapies that are not CYP1A2 inducers during treatment with bendamustine hydrochloride injection.

8 USE IN SPECIFIC POPULATIONS

8.1 Pregnancy

Risk Summary

In animal reproduction studies, intraperitoneal administration of bendamustine to pregnant mice and rats during organogenesis at doses 0.6 to 1.8 times the maximum recommended human dose (MRHD) resulted in embryo-fetal and/or infant mortality, structural abnormalities, and alterations to growth (see Data). There are no available data on bendamustine hydrochloride use in pregnant women to evaluate for a drug-associated risk of major birth defects, miscarriage or adverse maternal or fetal outcomes. Advise pregnant women of the potential risk to a fetus.

The estimated background risk of major birth defects and miscarriage for the indicated population is unknown. All pregnancies have a background risk of birth defect, loss, or other adverse outcomes. In the U.S. general population, the estimated background risk of major birth defects and miscarriage in clinically recognized pregnancies is 2% to 4% and 15% to 20%, respectively.

Data

Animal Data

Bendamustine hydrochloride was intraperitoneally administered once to mice from 210 mg/m^2 (approximately 1.8 times the MRHD) during organogenesis and caused an increase in resorptions, skeletal and visceral malformations (exencephaly, cleft palates, accessory rib, and spinal deformities) and decreased fetal body weights. This dose did not appear to be maternally toxic and lower doses were not evaluated. Repeat intraperitoneal administration of bendamustine hydrochloride in mice on gestation days 7 to 11 resulted in an increase in resorptions from 75 mg/m^2 (approximately 0.6 times the MRHD) and an increase in abnormalities from 112.5 mg/m^2 (approximately 0.9 times the MRHD), similar to those seen after a single intraperitoneal administration.

Bendamustine hydrochloride was intraperitoneally administered once to rats from 120 mg/m^2 (approximately the MRHD) on gestation days 4, 7, 9, 11, or 13 and caused embryo and fetal lethality as indicated by increased resorptions and a decrease in live fetuses. A significant increase in external (effect on tail, head, and herniation of external organs [exomphalos]) and internal (hydronephrosis and hydrocephalus) malformations were seen in dosed rats.

8.2 Lactation

Risk Summary

There are no data on the presence of bendamustine hydrochloride or its metabolites in either human or animal milk, the effects on the breastfed child, or the effects on milk production. Because of the potential for serious adverse reactions in the breastfed child, advise women not to breastfeed during treatment with bendamustine hydrochloride injection, and for 1 week after the last dose.

8.3 Females and Males of Reproductive Potential

Bendamustine hydrochloride injection can cause embryo-fetal harm when administered to a pregnant woman [see Use in Specific Populations (8.1)].

Pregnancy Testing

Pregnancy testing is recommended for females of reproductive potential prior to initiation of treatment with bendamustine hydrochloride injection.

Contraception

Females

Advise female patients of reproductive potential to use effective contraception during treatment with bendamustine hydrochloride injection and for 6 months after the last dose.

Males

Based on genotoxicity findings, advise males with female partners of reproductive potential to use effective contraception during treatment with bendamustine hydrochloride injection and for 3 months after the last dose [see Nonclinical Toxicology (13.1)].

Infertility

Based on findings from clinical studies, bendamustine hydrochloride injection may impair male fertility. Impaired spermatogenesis, azoospermia, and total germinal aplasia have been reported in male patients treated with alkylating agents, especially in combination with other drugs. In some instances, spermatogenesis may return in patients in remission, but this may occur only several years after intensive chemotherapy has been discontinued. Advise patients of the potential risk to their reproductive capacities.

Based on findings from animal studies, bendamustine hydrochloride injection may impair male fertility due to an increase in morphologically abnormal spermatozoa. The long-term effects of bendamustine hydrochloride injection on male fertility, including the reversibility of adverse effects, have not been studied [see Nonclinical Toxicology (13.1)].

8.4 Pediatric Use

Safety and effectiveness in pediatric patients have not been established.

Safety, pharmacokinetics and efficacy were assessed in a single open-label trial (NCT01088984) in patients aged 1 to 19 years with relapsed or refractory acute leukemia, including 27 patients with acute lymphocytic leukemia (ALL) and 16 patients with acute myeloid leukemia (AML). Bendamustine hydrochloride was administered as an intravenous infusion over 60 minutes on Days 1 and 2 of each 21-day cycle. There was no treatment response (CR+ CRp) in any patient. The safety profile in these patients was consistent with that seen in adults, and no new safety signals were identified.

The pharmacokinetics of bendamustine in 43 patients, aged 1 to 19 years (median age of 10 years) were within range of values previously observed in adults given the same dose based on body surface area.

8.5 Geriatric Use

No overall differences in safety were observed between patients ≥65 years of age and younger patients. No overall differences in efficacy in patients with non-Hodgkin Lymphoma were observed between geriatric patients and younger patients.

8.6 Renal Impairment

Do not use bendamustine hydrochloride injection in patients with creatinine clearance (CLcr) < 30 mL/min. [see Clinical Pharmacology (12.3)]

8.7 Hepatic Impairment

Do not use bendamustine hydrochloride injection in patients with AST or ALT 2.5 to 10 × upper limit of normal (ULN) and total bilirubin 1.5 to 3 × ULN, or total bilirubin > 3 × ULN [see Clinical Pharmacology (12.3)]

10 OVERDOSAGE

The intravenous LD50 of bendamustine hydrochloride is 240 mg/m^2 in the mouse and rat. Toxicities included sedation, tremor, ataxia, convulsions and respiratory distress.

Across all clinical experience, the reported maximum single dose received was 280 mg/m^2. Three of four patients treated at this dose showed ECG changes considered dose-limiting at 7 and 21 days post-dosing. These changes included QT prolongation (one patient), sinus tachycardia (one patient), ST and T wave deviations (two patients) and left anterior fascicular block (one patient). Cardiac enzymes and ejection fractions remained normal in all patients.

No specific antidote for bendamustine hydrochloride overdose is known. Management of overdosage should include general supportive measures, including monitoring of hematologic parameters and ECGs.

11 DESCRIPTION

Bendamustine hydrochloride is an alkylating agent. The chemical name of bendamustine hydrochloride is 1H-benzimidazole-2-butanoic acid, 5-[bis(2-chloroethyl)amino]-1 methyl-, monohydrochloride, monohydrate. Its empirical molecular formula is C16H21Cl2N3O2· HCl. H2O, and the molecular weight is 412.74 g/mol. Bendamustine hydrochloride contains a mechlorethamine group and a benzimidazole heterocyclic ring with a butyric acid substituent, and has the following structural formula:

Bendamustine hydrochloride injection for intravenous use is supplied as a sterile, clear, and colorless to yellow solution in a multiple-dose clear glass vial. Each milliliter contains 25 mg of bendamustine hydrochloride, USP, 38 mg (3.8%) absolute ethanol, 5 mg monothioglycerol, NF in polyethylene glycol 400, and 0.08 mg sodium hydroxide is used to adjust the acidity of polyethylene glycol 400 NF. Each mL contains 25 mg Bendamustine hydrochloride, which is equivalent to 22.7 mg Bendamustine free base.

12 CLINICAL PHARMACOLOGY

12.1 Mechanism of Action

Bendamustine is a bifunctional mechlorethamine derivative containing a purine-like benzimidazole ring. Mechlorethamine and its derivatives form electrophilic alkyl groups. These groups form covalent bonds with electron-rich nucleophilic moieties, resulting in interstrand DNA crosslinks. The bifunctional covalent linkage can lead to cell death via several pathways. Bendamustine is active against both quiescent and dividing cells. The exact mechanism of action of bendamustine remains unknown.

12.2 Pharmacodynamics

Based on the pharmacokinetics/pharmacodynamics analyses of data from adult NHL patients, nausea increased with increasing bendamustine Cmax.

Cardiac Electrophysiology

The effect of bendamustine on the QTc interval was evaluated in 53 patients with indolent NHL and mantle cell lymphoma on Day 1 of Cycle 1 after administration of rituximab at 375 mg/m^2 intravenous infusion followed by a 30-minute intravenous infusion of bendamustine at 90 mg/m^2/day. No mean changes greater than 20 milliseconds were detected up to one hour post infusion. The potential for delayed effects on the QT interval after one hour was not evaluated.

12.3 Pharmacokinetics

Absorption

Following a single IV dose of bendamustine hydrochloride Cmax typically occurred at the end of infusion. The dose proportionality of bendamustine has not been studied.

Distribution

The protein binding of bendamustine ranged from 94% to 96% and was concentration independent from 1 to 50 mcg/mL. The blood to plasma concentration ratios in human blood ranged from 0.84 to 0.86 over a concentration range of 10 to 100 mcg/mL.

The mean steady-state volume of distribution (Vss) of bendamustine was approximately 20 to 25 L.

Elimination

After a single intravenous dose of 120 mg/m^2 of bendamustine over 1 hour, the intermediate half-life (t½) of the parent compound is approximately 40 minutes. The mean terminal elimination t½ of two active metabolites, γ-hydroxybendamustine (M3) and N-desmethylbendamustine (M4) are approximately 3 hours and 30 minutes, respectively. Bendamustine clearance in humans is approximately 700 mL/min.

Metabolism

Bendamustine is extensively metabolized via hydrolytic, oxidative, and conjugative pathways. Bendamustine is primarily metabolized via hydrolysis to monohydroxy (HP1) and dihydroxy-bendamustine (HP2) metabolites with low cytotoxic activity in vitro. Two active minor metabolites, M3 and M4, are primarily formed via CYP1A2 in vitro. M3 and M4 concentrations of these metabolites in plasma are 1/10th and 1/100th that of the parent compound, respectively.

Excretion

Following IV infusion of radiolabeled bendamustine hydrochloride in cancer patients, approximately 76% of the dose was recovered. Approximately 50% of the dose was recovered in the urine (3.3% unchanged) and approximately 25% of the dose was recovered in the feces. Less than 1% of the dose was recovered in the urine as M3 and M4, and less than 5% of the dose was recovered in the urine as HP2.

Specific Populations

No clinically meaningful effects on the pharmacokinetics of bendamustine were observed based on age (31 to 84 years), sex, mild to moderate renal impairment (CLcr ≥ 30 mL/min), or hepatic impairment with total bilirubin 1.5 < ULN and AST or ALT < 2.5 × ULN. The effects of severe renal impairment (CLcr < 30 mL/min), or hepatic impairment with total bilirubin 1.5-3 × ULN and AST or ALT 2.5-10 × ULN or total bilirubin > 3 × ULN on the pharmacokinetics of bendamustine is unknown.

Race/Ethnicity

Exposures in Japanese subjects (n=6) were 40% higher than that in non-Japanese subjects receiving the same dose. The clinical importance of this difference on the safety and efficacy of bendamustine hydrochloride in Japanese subjects has not been established.

Drug Interaction Studies

In Vitro Studies

Effect of Bendamustine on CYP Substrates

Bendamustine did not inhibit CYP1A2, 2C9/10, 2D6, 2E1, or 3A4/5. Bendamustine did not induce metabolism of CYP1A2, CYP2A6, CYP2B6, CYP2C8, CYP2C9, CYP2C19, CYP2E1, or CYP3A4/5.

Effect of Transporters on Bendamustine Hydrochloride

Bendamustine is a substrate of P-glycoprotein and breast cancer resistance protein (BCRP).

13 NONCLINICAL TOXICOLOGY

13.1 Carcinogenesis, Mutagenesis, Impairment of Fertility

Bendamustine was carcinogenic in mice. After intraperitoneal injections at 37.5 mg/m^2/day (the lowest dose tested, approximately 0.3 times the maximum recommended human dose [MRHD]) and 75 mg/m^2/day (approximately 0.6 times the MRHD) for 4 days, peritoneal sarcomas in female AB/jena mice were produced. Oral administration at 187.5 mg/m^2/day (the only dose tested, approximately 1.6 times the MRHD) for 4 days induced mammary carcinomas and pulmonary adenomas.

Bendamustine is a mutagen and clastogen. In a reverse bacterial mutation assay (Ames assay), bendamustine was shown to increase revertant frequency in the absence and presence of metabolic activation. Bendamustine was clastogenic in human lymphocytes in vitro, and in rat bone marrow cells in vivo (increase in micronucleated polychromatic erythrocytes) from 37.5 mg/m^2 (the lowest dose tested, approximately 0.3 times the MRHD).

Bendamustine induced morphologic abnormalities in spermatozoa in mice. Following tail vein injection of bendamustine at 120 mg/m^2 or a saline control on days 1 and 2 for a total of 3 weeks, the number of spermatozoa with morphologic abnormalities was 16% higher in the bendamustine-treated group as compared to the saline control group.

14 CLINICAL STUDIES

The efficacy of bendamustine hydrochloride was evaluated in a single arm study of 100 patients with indolent B-cell NHL that had progressed during or within six months of treatment with rituximab or a rituximab-containing regimen. Patients were included if they relapsed within 6 months of either the first dose (monotherapy) or last dose (maintenance regimen or combination therapy) of rituximab. All patients received bendamustine hydrochloride intravenously at a dose of 120 mg/m^2, on Days 1 and 2 of a 21-day treatment cycle. Patients were treated for up to 8 cycles.

The median age was 60 years, 65% were male, and 95% had a baseline WHO performance status of 0 or 1. Major tumor subtypes were follicular lymphoma (62%), diffuse small lymphocytic lymphoma (21%), and marginal zone lymphoma (16%). Ninety-nine percent of patients had received previous chemotherapy, 91% of patients had received previous alkylator therapy, and 97% of patients had relapsed within 6 months of either the first dose (monotherapy) or last dose (maintenance regimen or combination therapy) of rituximab.

Efficacy was based on the assessments by a blinded independent review committee (IRC) and included overall response rate (complete response + complete response unconfirmed + partial response) and duration of response (DR) as summarized in Table 6.

Table 6: Efficacy Data for NHL*

 | Bendamustine Hydrochloride (N=100)
Response Rate (%)
Overall response rate (CR+CRu+PR) | 74
(95% CI) | (64.3, 82.3)
Complete response (CR) | 13
Complete response unconfirmed (CRu) | 4
Partial response (PR) | 57
Duration of Response (DR)
Median, months (95% CI) | 9.2 months (7.1, 10.8)

CI = confidence interval

*IRC assessment was based on modified International Working Group response criteria (IWG-RC). Modifications to IWG-RC specified that a persistently positive bone marrow in patients who met all other criteria for CR would be scored as PR. Bone marrow sample lengths were not required to be ≥20 mm

15 REFERENCES

1. OSHA Hazardous Drugs. OSHA. [http://www.osha.gov/SLTC/hazardousdrugs/index.html]

16 HOW SUPPLIED/STORAGE AND HANDLING

Safe Handling and Disposal

Bendamustine hydrochloride injection is a hazardous drug. Follow applicable special handling and disposal procedures^1. Care should be exercised in the handling and preparation of solutions prepared from bendamustine hydrochloride injection. The use of gloves and safety glasses is recommended to avoid exposure in case of breakage of the vial or other accidental spillage. If gloves come in contact with bendamustine hydrochloride injection prior to dilution, remove gloves and follow disposal procedures^1. If a solution of bendamustine hydrochloride injection contacts the skin, wash the skin immediately and thoroughly with soap and water. If bendamustine hydrochloride injection contacts the mucous membranes, flush thoroughly with water.

How Supplied

Bendamustine hydrochloride injection is supplied in individual cartons of clear multiple-dose vials containing 100 mg of bendamustine hydrochloride as a clear, and colorless to yellow solution.

NDC 60505-6228-0: 100 mg/4 mL (25 mg/mL).

Storage

Store bendamustine hydrochloride injection in refrigerator, 2ºC to 8ºC (36ºF to 46ºF). Retain in original carton until contents are used to protect from light.

17 PATIENT COUNSELING INFORMATION

Myelosuppression

Inform patients of the likelihood that bendamustine hydrochloride injection will cause a decrease in white blood cells, platelets, and red blood cells, and the need for frequent monitoring of blood counts. Advise patients to report shortness of breath, significant fatigue, bleeding, fever, or other signs of infection [see Warnings and Precautions (5.1)].

Progressive Multifocal Leukoencephalopathy (PML)

Inform patients to immediately contact their healthcare provider if they experience confusion, memory loss, trouble thinking, difficulty talking or walking, vision loss or other neurological or cognitive symptoms [see Warnings and Precautions (5.3)].

Anaphylaxis and Infusion Reactions

Inform patients of the possibility of serious or mild allergic reactions and to immediately report rash, facial swelling, or difficulty breathing during or soon after infusion. [see Warnings and Precautions (5.4)]

Skin Reactions

Advise patients that a rash or itching may occur during treatment with bendamustine hydrochloride injection. Advise patients to immediately report severe or worsening rash or itching. [see Warnings and Precautions (5.6)]

Hepatotoxicity

Inform patients of the possibility of developing liver function abnormalities and serious hepatic toxicity. Advise patients to immediately contact their health care provider if signs of liver failure occur, including jaundice, anorexia, bleeding or bruising [see Warnings and Precautions (5.7)].

Fatigue

Advise patients that bendamustine hydrochloride injection may cause tiredness and to avoid driving any vehicle or operating any dangerous tools or machinery if they experience this side effect [see Adverse Reactions (6.1)].

Nausea and Vomiting

Advise patients that bendamustine hydrochloride injection may cause nausea and/or vomiting. Patients should report nausea and vomiting so that symptomatic treatment may be provided [see Adverse Reactions (6.1)].

Diarrhea

Advise patients that bendamustine hydrochloride injection may cause diarrhea. Patients should report diarrhea to the physician so that symptomatic treatment may be provided [see Adverse Reactions (6.1)].

Non-melanoma Skin Cancer (NMSC)

Advise patients to undergo regular skin cancer screenings, and to report any suspicious skin changes to their healthcare provider [see Warnings and Precautions (5.8)].

Embryo-Fetal Toxicity

Advise pregnant women and females of reproductive potential of the potential risk to a fetus. Advise females to inform their healthcare provider of a known or suspected pregnancy [see Warnings and Precautions (5.10), Use in Specific Populations (8.1, 8.3), and Nonclinical Toxicology (13.1)]. Advise female patients of reproductive potential to use effective contraception during treatment with bendamustine hydrochloride injection and for 6 months after the last dose [see Use in Specific Populations (8.1, 8.3)]. Advise males with female partners of reproductive potential to use effective contraception during treatment with bendamustine hydrochloride injection and for 3 months after the last dose [see Use in Specific Populations (8.3), and Nonclinical Toxicology (13.1)].

Lactation

Advise females not to breastfeed during treatment with bendamustine hydrochloride injection and for 1 week after the last dose [see Use in Specific Populations (8.2)].

Infertility

Advise males of reproductive potential that bendamustine hydrochloride injection may impair fertility [see Use in Specific Populations (8.3)].

Manufactured by: | Manufactured for:
MSN Laboratories Private Limited, India | Apotex Corp.
ML No. 5/MN/TS/2014/F/G | Weston, Florida USA 33326

Rev 3